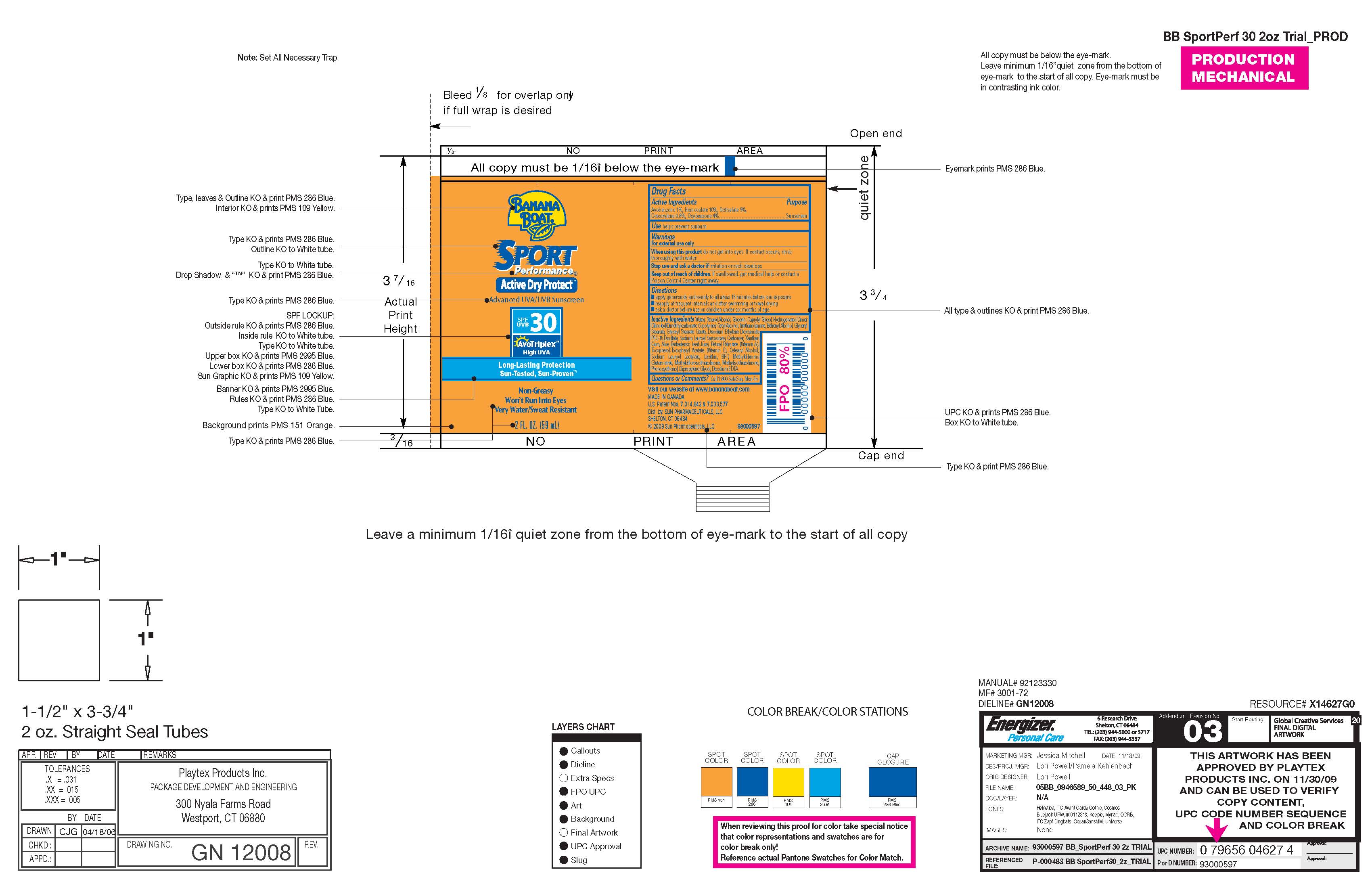 DRUG LABEL: Banana Boat Sport Performance
NDC: 61047-810 | Form: LOTION
Manufacturer: KIK Custom Products
Category: otc | Type: HUMAN OTC DRUG LABEL
Date: 20100312

ACTIVE INGREDIENTS: Avobenzone 0.58 mL/58 mL; Homosalate 5.8 mL/58 mL; Octisalate 2.9 mL/58 mL; Octocrylene 0.464 mL/58 mL; Oxybenzone 2.32 mL/58 mL

Banana Boat Sport Performance Active Dry Protect Advance UVA/UVB Sunscreen SPF 30 Long Lasting Proctection, Sun Tested, Sun Proven

Drug Facts:
Avobenzone: 1%
Homosalate: 15%
Octisalate: 5%
Octicrylene: 0.8%
Oxybenzone: 2%
Purpose: Sunscreen

WARNINGS

FOR EXTERNAL USE ONLY.
WHEN USING THIS PRODUCT, DO NOT GET INTO EYES IF CONTACT OCCURS, RINSE THOROUGHLY WITH WATER.
STOP USE AND ASK DOCTOR IS IRRITATION OR RASH DEVELOPS. KEEP OUT OF REACH OF CHILDREN.
IF SWALLOWED, GET MEDICAL HELP OR CONTACT POISON CONTROL CENTER RIGHT AWAY.

INACTIVE INGREDIENT

Water, Cetearyl Alcohol, Glycerin, Capryly Glycol, Hydrogenated Dimer Dilnoleyl/Dimethyl Carbonate,
Copolymer, Cetyl Alcohol, Triethanolamine, Behenyl Acohol, Glyceryl Stearate, Glyceryl Stearate, Citrate,
Disodium Ethylene, Dicocamide PEG-15 Disulfate, Sodium Lauroyl Sarcosinate, Carbomer, Xanthan Gum,
Aloe Barbadensis Leaf Juice, Retinyl Palmitate (Vitamin A), Tocopherol, Tocopheryl Acetate (Vitamin E),
Cetearyl Alchol, Sodium Lauroyl, Lactylate, Lecithin, BHT, Methyl Dibromo Glutaronitrile, Methyl Chloisothiazolinone.
Methyl Isothiazolinone, Phenoxy Ethanol, Dipropylene Glycol, Disodium EDTA

Questions or Comments: Call 1-800-SAFESUN Mon-Fri.